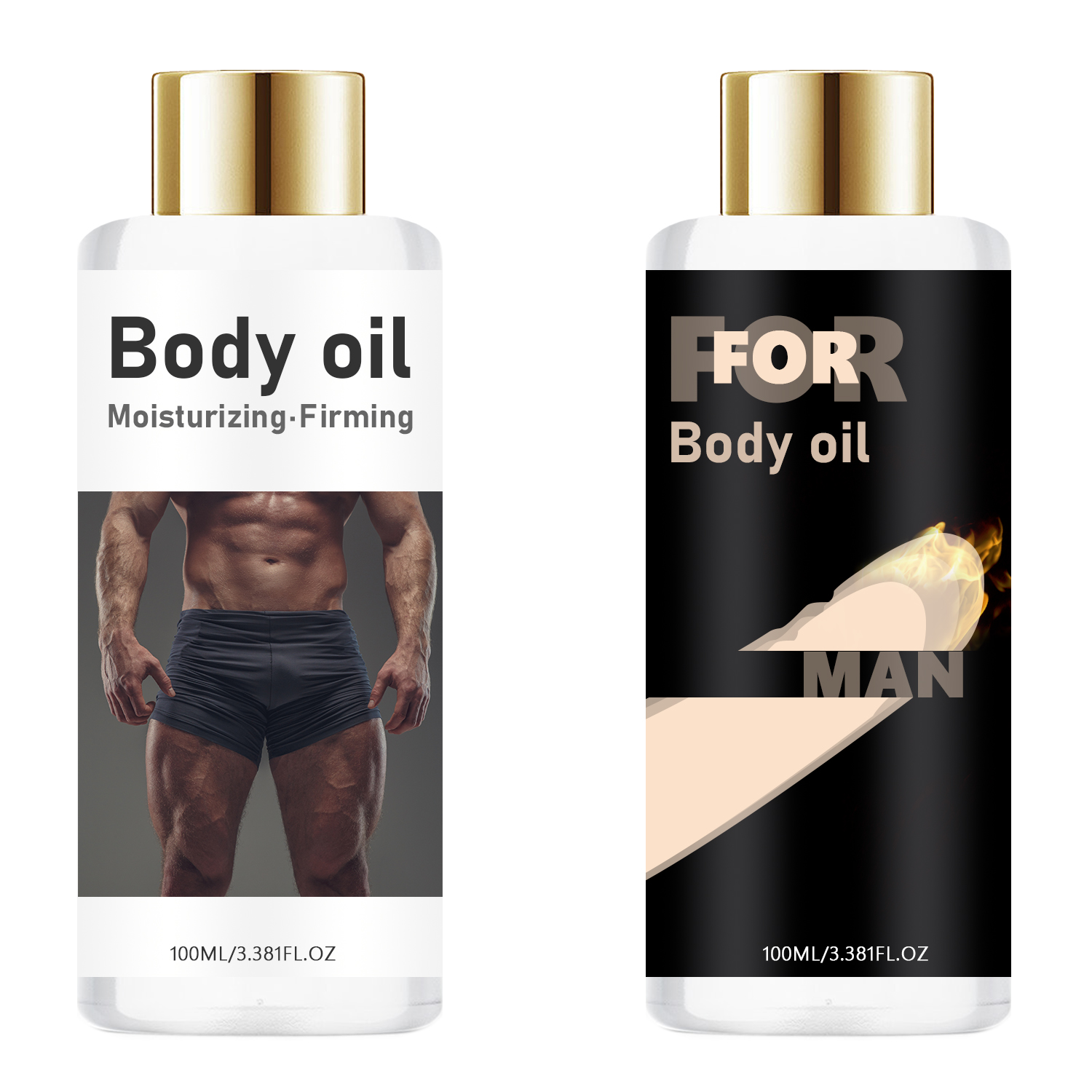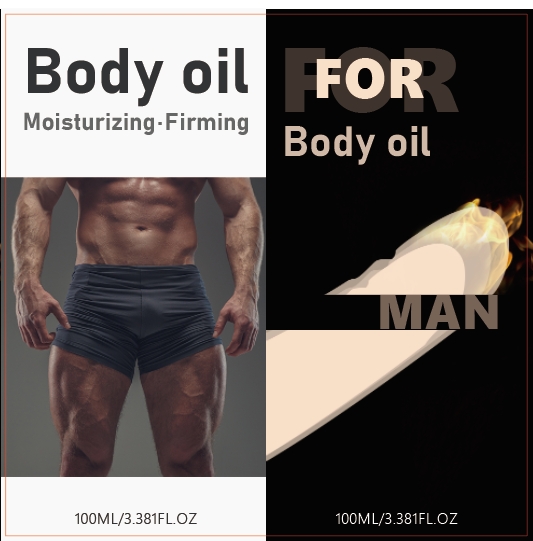 DRUG LABEL: Body Oil
NDC: 84025-222 | Form: OIL
Manufacturer: Guangzhou Yanxi Biotechnology Co., Ltd
Category: otc | Type: HUMAN OTC DRUG LABEL
Date: 20241019

ACTIVE INGREDIENTS: PANTHENOL 3 mg/100 mL; GLYCERIN 5 mg/100 mL
INACTIVE INGREDIENTS: WATER

DOSAGE AND ADMINISTRATION

USE AS BADY

WARNINGS

keep out of children

INACTIVE INGREDIENT

Aqua

INDICATIONS AND USAGE

Use for massage to achieve premium relaxation, nourishment, and skin moisturization. Suitable for professional or home use.

keep out of children

PURPOSE

helps moisturize dry skin and can improve your connection.